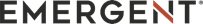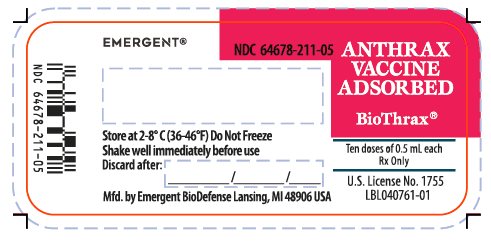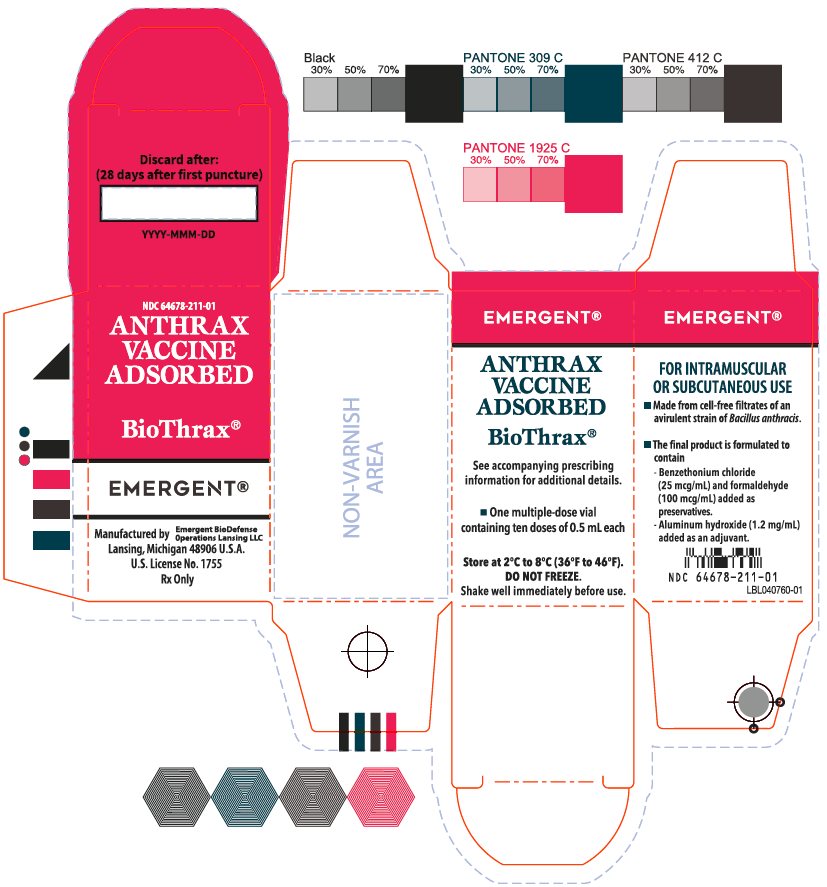 DRUG LABEL: BioThrax
NDC: 64678-211 | Form: INJECTION, SUSPENSION
Manufacturer: Emergent BioDefense Operations Lansing, LLC
Category: other | Type: VACCINE LABEL
Date: 20260123

ACTIVE INGREDIENTS: BACILLUS ANTHRACIS STRAIN V770-NP1-R ANTIGENS 100 ug/1 mL
INACTIVE INGREDIENTS: ALUMINUM HYDROXIDE 1.2 mg/1 mL; SODIUM CHLORIDE 8.5 mg/1 mL; FORMALDEHYDE 100 ug/1 mL; BENZETHONIUM CHLORIDE 25 ug/1 mL; WATER

HIGHLIGHTS OF PRESCRIBING INFORMATION

These highlights do not include all the information needed to use BIOTHRAX safely and effectively. See full prescribing information for BIOTHRAX.
BIOTHRAX® (Anthrax Vaccine Adsorbed) injectable suspension, for intramuscular or subcutaneous use
Initial U.S. Approval: 1970

1 INDICATIONS AND USAGE

BioThrax is a vaccine indicated for the active immunization for the prevention of disease caused by Bacillus anthracis in persons 18 through 65 years of age.
BioThrax is approved for:

- Pre-exposure prophylaxis of disease in persons at high risk of exposure.
- Post-exposure prophylaxis of disease following suspected or confirmed Bacillus anthracis exposure, when administered in conjunction with recommended antibacterial drugs.

The efficacy of BioThrax for post-exposure prophylaxis is based solely on studies in animal models of inhalational anthrax. (1)

2 DOSAGE AND ADMINISTRATION

For intramuscular or subcutaneous use (2).

Each dose is 0.5 mL.
Pre-Exposure Prophylaxis (2.1):

Schedule | Route of Administration | Dosing Schedule
Primary Series | Intramuscular | 0,1, and 6 months
Booster Series | Intramuscular | 6 and 12 months after completion of the primary series and at 12-month intervals thereafter

In persons who are at risk for hematoma formation following intramuscular injection, BioThrax may be administered by the subcutaneous route. The pre-exposure prophylaxis schedule for BioThrax administered subcutaneously is 0, 2, 4 weeks, and 6 months with booster doses 6 and 12 months after completion of the primary series, and at 12-month intervals thereafter.
Post-Exposure Prophylaxis (2.1):

Schedule | Route of Administration | Dosing Schedule
Primary Series | Subcutaneous | 0, 2, and 4 weeks post-exposure combined with antimicrobial therapy

3 DOSAGE FORMS AND STRENGTHS

Injectable suspension. Each dose is 0.5 mL. (3)

4 CONTRAINDICATIONS

Severe allergic reaction (e.g. anaphylaxis) after a previous dose of BioThrax or a component of the vaccine. (4)

5 WARNINGS AND PRECAUTIONS

BioThrax can cause fetal harm when administered to a pregnant individual. If this drug is used during pregnancy, or if the patient becomes pregnant while taking this drug, the patient should be apprised of the potential hazard to a fetus. Weigh the potential benefits of vaccination against the potential risk to the fetus. (5.3)
The stopper of the vial contains natural rubber latex and may cause allergic reactions in latex sensitive individuals. (5.2)

6 ADVERSE REACTIONS

The most common (≥10%) local (injection-site) adverse reactions observed in clinical studies were tenderness, pain, erythema, edema, and arm motion limitation. The most common (≥5%) systemic adverse reactions were muscle aches, fatigue, and headache. (6)

To report SUSPECTED ADVERSE REACTIONS, contact Emergent BioSolutions at 1-800-768-2304 or medicalinformation@ebsi.com or VAERS at 1-800-822-7967 or www.vaers.hhs.gov.

FULL PRESCRIBING INFORMATION

1 INDICATIONS AND USAGE

BioThrax is a vaccine indicated for the active immunization for the prevention of disease caused by Bacillus anthracis in persons 18 through 65 years of age.

- BioThrax is approved for pre-exposure prophylaxis of disease in persons whose occupation or other activities place them at high risk of exposure.
- BioThrax is approved for post-exposure prophylaxis of disease following suspected or confirmed Bacillus anthracis exposure, when administered in conjunction with recommended antibacterial drugs.

The efficacy of BioThrax for post-exposure prophylaxis is based solely on studies in animal models of inhalational anthrax.

2 DOSAGE AND ADMINISTRATION

For intramuscular or subcutaneous use.

2.1 Dose

Each dose is 0.5 mL.

Pre-Exposure Prophylaxis:

Schedule | Route of Administration | Dosing Schedule
Primary Series | Intramuscular | 0,1, and 6 months
Booster Series | Intramuscular | 6 and 12 months after completion of the primary series and at 12-month intervals thereafter

In persons who are at risk for hematoma formation following intramuscular injection, BioThrax may be administered by the subcutaneous route. The pre-exposure prophylaxis schedule for BioThrax administered subcutaneously is 0, 2, 4 weeks, and 6 months with booster doses at 6 and 12 months after completion of the primary series and at 12-month intervals thereafter.

The optimal schedule for catch up of missed or delayed booster doses is unknown. [see Clinical Studies (14)]

Post-Exposure Prophylaxis:

Schedule | Route of Administration | Dosing Schedule
Primary Series | Subcutaneous | 0, 2, and 4 weeks post-exposure combined with antimicrobial therapy

2.2 Administration

Shake the vial thoroughly to ensure that the suspension is homogeneous during withdrawal. Parenteral drug products should be inspected visually for particulate matter and discoloration prior to administration, whenever solution and container permit. If either of these conditions exists, do not administer the vaccine and discard the vial. Once the stopper of the multiple-dose vial has been pierced, discard the vial within 28 days [see How Supplied/Storage and Handling (16)].

Administer pre-exposure prophylaxis vaccinations intramuscularly into the deltoid muscle. If pre-exposure prophylaxis requires subcutaneous administration, administer over the deltoid muscle. Administer post-exposure prophylaxis vaccinations subcutaneously over the deltoid muscle.

3 DOSAGE FORMS AND STRENGTHS

BioThrax is an injectable suspension. Each dose is 0.5 mL.

4 CONTRAINDICATIONS

Do not administer BioThrax to individuals with a history of anaphylactic or anaphylactic-like reaction following a previous dose of BioThrax or any component of the vaccine, including aluminum, benzethonium chloride, and formaldehyde. [see Description (11)]

5 WARNINGS AND PRECAUTIONS

5.1 Hypersensitivity Reactions

Acute allergic reactions, including anaphylaxis, have occurred with BioThrax. Appropriate medical treatment and supervision must be available to manage possible anaphylactic reactions following administration of the vaccine. [see Contraindications (4)]

5.2 Latex

The stopper of the vial contains natural rubber latex and may cause allergic reactions to patients with a possible history of latex sensitivity. [see How Supplied/Storage and Handling (16)]

5.3 Pregnancy

BioThrax can cause fetal harm when administered to a pregnant woman. If this drug is used during pregnancy, or if the patient becomes pregnant while taking this drug, the patient should be apprised of the potential hazard to a fetus. Weigh the potential benefits of vaccination against the potential risk to the fetus. [see Use in Specific Populations (8.1)]

If BioThrax is administered during pregnancy, the vaccinated individual should be apprised of the potential hazard to a fetus.

5.4 History of Anthrax Disease

History of anthrax disease may increase the potential for severe local adverse reactions.

5.5 Altered Immunocompetence

If BioThrax is administered to immunocompromised persons, including those receiving immunosuppressive therapy, the immune response may be diminished.

5.6 Limitations of Vaccine Effectiveness

Vaccination with BioThrax may not protect all individuals.

6 ADVERSE REACTIONS

The most common (≥10%) local (injection-site) adverse reactions observed in clinical studies were tenderness, pain, erythema, edema, and arm motion limitation. The most common (≥5%) systemic adverse reactions were muscle aches, headache, and fatigue.

6.1 Clinical Trials Experience

Because clinical trials are conducted under widely varying conditions, adverse reaction rates observed in the clinical trials of a product cannot be directly compared to rates in the clinical trials of another product and may not reflect the rates observed in clinical practice.
Pre-Exposure Prophylaxis

In an open-label safety study of 15,907 doses of BioThrax administered by the subcutaneous route to approximately 7,000 textile employees, laboratory workers and other at risk individuals, local and systemic reactions were monitored. Over the course of the 5-year study the following local adverse reactions were reported: 24 (0.15% of doses administered) severe local adverse reactions (defined as edema or induration measuring greater than 120 mm in diameter or accompanied by marked limitation of arm motion or marked axillary node tenderness), 150 (0.94% of doses administered) moderate local adverse reactions (edema or induration greater than 30 mm but less than 120 mm in diameter), and 1,373 (8.63% of doses administered) mild local adverse reactions (erythema only or induration measuring less than 30 mm in diameter). Four cases of systemic adverse reactions were reported during the 5-year reporting period (<0.06% of doses administered). These reactions, which were reported to have been transient, included fever, chills, nausea, and general body aches.

In a randomized, double-blinded, placebo-controlled, and active-controlled multi-center clinical study, 1,564 healthy subjects were enrolled. The objective of this study was to evaluate the effect of (1) changing the route of vaccine administration from subcutaneous (SC) to intramuscular (IM), and (2) of reducing the number of doses on the safety and immunogenicity of BioThrax. The dosing schedules and routes studied are provided in Table 1. [see Clinical Studies (14)]

Group A (8SC) (N=259) received BioThrax via the SC route of administration at Weeks 0, 2, 4, and Months 6, 12, 18 followed by 2 annual boosters (original U.S. licensed route/schedule). Group A served as the active control in this study.
Group B (8IM) (N=262) received BioThrax via the IM route of administration at Weeks 0, 2, 4, and Months 6, 12, 18 followed by 2 annual boosters.
Group C (COM) (N=782) received BioThrax via the IM route of administration at Weeks 0, 4 (no Week 2 dose), and Month 6 with various schedules thereafter. (Group C represents data from 3 randomized groups [Groups D, E, and F] combined for the analysis through Month 7 because the schedules are identical through the Month 6 dose.)
Group D (7IM) (N=256) received BioThrax via the IM route of administration at Weeks 0, 4 (no Week 2 dose), and Months 6, 12, 18 followed by 2 annual boosters.
Group E (5IM) (N=258) received BioThrax via the IM route of administration at Weeks 0, 4 (no Week 2 dose), and Months 6, 18 followed by 1 booster dose at Month 42 (2 year interval).
Group F (4IM) (N=268) received BioThrax via the IM route of administration at Weeks 0, 4 (no Week 2 dose), and Month 6 followed by 1 booster dose at Month 42 (3 year interval).

Table 1 Vaccination Schedules and Routes Evaluated
Group/Route | WK 0 | WK 2 | WK 4 | MO 6 | MO 12 | MO 18 | MO 30 | MO 42
Group A (8SC)a | V | V | V | V | V | V | V | V
Group B (8IM) | V | V | V | V | V | V | V | V
Group D (7IM) | V | S | V | V | V | V | V | V
Group E (5IM) | V | S | V | V | S | V | S | V
Group F (4IM) | V | S | V | V | S | S | S | V
Placebob | S | S | S | S | S | S | S | S
WK = Week; MO = Month; SC = subcutaneous; IM = intramuscular; V = vaccine; S = saline
a Active Control.
b Subjects randomized to the control group were then re-randomized (1:1) to receive saline by the IM or SC route. The IM and SC placebo groups are combined in analyses.

Subjects were instructed to complete a 14-day post-vaccination diary card after the first 2 doses and a 28-day diary card after the subsequent doses to capture solicited and unsolicited adverse reactions. Adverse reaction data were also collected from in-clinic exams, which were performed prior to, and 15 to 60 minutes after each injection, at 1 to 3 days after each injection for the first two injections, and at 28 days after injections 3 through 8. The mean age, gender ratio, and race distribution were not significantly different across treatment groups among the vaccinated cohort (N=1563). The mean age was 39 years (range 18 to 62 years). Fifty-one percent of participants were female and 49% were male. Seventy-four percent were white, 21% were black and 5% were categorized as “other”.

Shown in Table 2 are the rates (percentage) of prospectively defined local and systemic solicited adverse reactions observed in the in-clinic exams for doses 1-4 as well as the rates (percentage) of local and systemic solicited adverse reactions observed in the in-clinic exams for doses 5-8.

Analysis of injection site (local) adverse reactions by study group was performed after each dose. It was observed that groups receiving BioThrax by the IM route had a statistically significantly lower incidence (p ≤ 0.05) of any (one or more) local adverse reactions compared with the BioThrax SC route, by dose in the in-clinic data set, in 23 out of 24 analyses. (This excludes doses where IM groups received a placebo.) Individual injection site adverse reactions occurring at statistically significantly lower frequencies (p ≤ 0.05) in participants given BioThrax by the IM route included warmth (in all analyses), tenderness (in 19 out of 24 analyses), itching (in 22 out of 24 analyses), erythema (in all analyses), induration (in all analyses), edema (in 20 out of 24 analyses), and nodule (in all analyses). However, by dose, the incidences of arm motion limitation were comparable or higher in each BioThrax IM group compared with the 8SC group, with statistically significantly higher incidences (p ≤ 0.05) observed in 10 out of 24 analyses. The incidence of any moderate or severe local adverse reactions was lower in BioThrax IM groups, compared with the 8SC group after each dose. Route of administration did not affect the occurrence of systemic adverse reactions, with the exception of muscle ache (increased incidence in the BioThrax IM groups after most doses). There was no pattern for differences in the incidence of any moderate or severe systemic adverse reactions for BioThrax IM groups compared with the 8SC group after each dose. The proportion of participants with severe local or systemic adverse reactions reported by adverse reaction category after each dose was very low (generally <1%).

Overall, women had a higher incidence of any local adverse reaction than did men, by dose, within BioThrax groups, regardless of the route of administration. Overall, women also had a higher incidence of any systemic adverse reaction than men, within BioThrax groups, regardless of the route of administration. A brief pain or burning sensation, felt immediately after vaccine injection, and distinct from injection site pain, was reported by 45 - 97% of all study participants receiving BioThrax. Reporting frequency and event intensity varied with route of administration and vaccine dose. Up to 11% of subjects rated the brief pain or burning they experienced immediately after vaccine injection as 8 out of 10 or greater. Female participants generally experienced a higher pain scale rating than male participants.

Eight serious adverse events (SAEs) were reported with 6 subjects and determined to be possibly related to the administration of BioThrax: (1) a case of generalized allergic reaction, (2) a case of ANA positive autoimmune disorder manifesting as a moderate bilateral arthralgia of the metacarpophalangeal (MCP) joints, (3) a right shoulder supraspinatus tendon tear, (4) a case of bilateral pseudotumor cerebri with bilateral disc edema, (5) a case of generalized seizure and hospitalization for evaluation of hydrocephalus and endoscopic fluid ventriculostomy, (6) a case of bilateral ductal carcinoma of the breast. No SAEs were determined by the investigator to be probably or definitely related to administration of BioThrax. The percent of serious adverse events was similar between the BioThrax combined groups (193/1303 or 15%) and the placebo group (38/260 or 15%).

Fifty-one pregnancies were reported in this study, 33 of which occurred in women who received BioThrax as their last dose prior to conception and 18 in women who received placebo as their last dose prior to conception. Pregnancy outcomes where BioThrax was given within 30 days prior to conception (n=5) were 3 full-term live births (including 1 healthy term infant with a mild right clubbed foot abnormality), 1 spontaneous abortion, and 1 first trimester intra-utero fetal death. Pregnancy outcomes in the placebo group (n=5) were 4 full-term live births (including one with bilateral congenital hip dysplasia) and 1 elective abortion.

Table 2 Adverse Reactions: In-Clinic Day 0 – 3, Solicited by Dose Numbera
 | Group D; BioThrax 7IM; (BioThrax Doses 1, 3-8) Weeks-0-4-26b; Months 12-18-30-42 |  |  |  |  |  |  |  | Placeboc; Control SC/IM; (Doses 1-8) Weeks-0-2-4-26; Months 12-18-30-42 |  |  |  |  |  |  |  | Group A; BioThrax 8SC; (BioThrax Doses 1-8) Weeks-0-2-4-26; Months 12-18-30-42
Number of Subjects (N)d | 256 |  |  |  |  |  |  |  | 260 |  |  |  |  |  |  |  | 259
 | Dose |  |  |  |  |  |  |  | Dose |  |  |  |  |  |  |  | Dose
 | 1 | 2b | 3 | 4 | 5 | 6 | 7 | 8 | 1 | 2 | 3 | 4 | 5 | 6 | 7 | 8 | 1 | 2 | 3 | 4 | 5 | 6 | 7 | 8
 | % | % | % | % | % | % | % | % | % | % | % | % | % | % | % | % | % | % | % | % | % | % | % | %
Local Adverse Reactions
Presence of any local adverse reaction | 60 | 23 | 68 | 68 | 69 | 77 | 76 | 73 | 22 | 22 | 19 | 27 | 25 | 29 | 25 | 18 | 81 | 89 | 80 | 84 | 81 | 84 | 84 | 92
Warmth | 4 | 1 | 8 | 10 | 11 | 13 | 14 | 19 | 1 | 0 | 0 | 0 | 0 | 0 | 1 | 1 | 29 | 41 | 32 | 39 | 34 | 40 | 51 | 49
Tenderness | 46 | 7 | 51 | 47 | 41 | 44 | 44 | 48 | 6 | 8 | 7 | 10 | 6 | 7 | 7 | 4 | 64 | 72 | 48 | 65 | 53 | 57 | 61 | 63
Itching | 1 | 0 | 2 | 4 | 7 | 7 | 7 | 10 | 0 | 0 | 0 | 0 | 1 | 0 | 0 | 0 | 3 | 16 | 23 | 20 | 17 | 22 | 25 | 26
Pain | 16 | 4 | 20 | 15 | 16 | 13 | 16 | 15 | 4 | 2 | 3 | 4 | 4 | 2 | 3 | 2 | 16 | 22 | 12 | 19 | 16 | 14 | 18 | 20
Arm motion limitation | 14 | 1 | 15 | 11 | 10 | 10 | 15 | 9 | 1 | 0 | 2 | 1 | 1 | 1 | 1 | 0 | 8 | 12 | 5 | 11 | 10 | 5 | 8 | 5
Erythema | 15 | 10 | 20 | 30 | 35 | 48 | 40 | 37 | 11 | 12 | 7 | 13 | 14 | 17 | 14 | 11 | 53 | 64 | 57 | 65 | 64 | 64 | 68 | 71
Induration | 7 | 7 | 12 | 16 | 21 | 23 | 15 | 17 | 1 | 3 | 2 | 3 | 4 | 4 | 3 | 3 | 26 | 35 | 28 | 40 | 38 | 36 | 38 | 35
Edema | 5 | 2 | 11 | 20 | 15 | 23 | 30 | 25 | 3 | 4 | 4 | 4 | 4 | 7 | 8 | 5 | 17 | 33 | 31 | 33 | 31 | 35 | 37 | 46
Nodule | 3 | 0 | 4 | 5 | 8 | 9 | 6 | 5 | 0 | 2 | 0 | 1 | 2 | 0 | 2 | 0 | 39 | 42 | 36 | 26 | 26 | 23 | 21 | 27
Bruise | 5 | 4 | 5 | 3 | 2 | 4 | 3 | 2 | 4 | 5 | 1 | 4 | 3 | 5 | 5 | 4 | 6 | 7 | 6 | 6 | 3 | 6 | 5 | 6
Presence of any moderate/severe local adverse reactionse | 5 | 1 | 8 | 7 | 4 | 5 | 6 | 4 | 0 | 0 | 0 | 0 | 0 | 0 | 0 | 0 | 7 | 16 | 8 | 13 | 10 | 7 | 12 | 14
Presence of any large local adverse reactionf | 0 | 0 | 0 | 2 | 2 | 4 | 2 | 2 | 0 | 0 | 0 | 0 | 0 | 0 | 0 | 0 | 0 | 1 | 4 | 2 | 1 | 2 | 2 | 4
Systemic Adverse Reactions
Presence of any systemic adverse reaction | 18 | 12 | 24 | 19 | 15 | 19 | 10 | 9 | 10 | 10 | 13 | 11 | 13 | 8 | 13 | 4 | 16 | 20 | 18 | 21 | 18 | 14 | 20 | 17
Fatigue | 9 | 4 | 12 | 10 | 9 | 11 | 4 | 6 | 5 | 4 | 7 | 7 | 8 | 5 | 10 | 3 | 9 | 12 | 8 | 12 | 12 | 10 | 10 | 13
Muscle ache | 8 | 4 | 13 | 6 | 5 | 5 | 3 | 5 | 2 | 2 | 3 | 4 | 5 | 3 | 1 | 1 | 5 | 8 | 4 | 5 | 4 | 3 | 9 | 5
Headache | 6 | 6 | 9 | 7 | 8 | 8 | 5 | 4 | 4 | 6 | 5 | 4 | 7 | 4 | 6 | 1 | 7 | 9 | 8 | 11 | 7 | 5 | 9 | 2
Fever >100.4°F | 0 | 0 | 0 | 0 | 0 | 0 | 0 | 0 | 0 | 0 | 0 | 0 | 1 | 0 | 0 | 0 | 0 | 0 | 0 | 0 | 0 | 0 | 0 | 0
Tender/painful axillary adenopathy | 0 | 0 | 0 | 1 | 1 | 1 | 0 | 0 | 0 | 0 | 0 | 0 | 0 | 0 | 0 | 1 | 0 | 1 | 2 | 1 | 1 | 0 | 1 | 0
Presence of any moderate/severe systemic adverse reactionsg | 2 | 2 | 6 | 3 | 3 | 5 | 4 | 3 | 1 | 2 | 2 | 1 | 3 | 1 | 2 | 1 | 2 | 5 | 4 | 3 | 3 | 2 | 3 | 2
a Per-dose, statistical assessment performed on Intent-to-Treat population data. Evaluations performed at 15-60 minutes and 1-3 days following each injection and prior to the next scheduled injection.
b Subjects received saline (instead of BioThrax) for the Week 2 dose. Placebo dose data for 7IM group is in italics.
c The two saline groups (SC and IM) were combined.
d N is the highest number per treatment arm (received at least one dose); denominator (N) varied with dose number due to attrition over time.
e Moderate = causes discomfort and interferes with normal daily activities; Severe = incapacitating and completely prevents performing normal daily activities. This is based on the local AE categories of warmth, tenderness, itching, pain, and arm motion limitation.
f Large = an occurrence of induration, erythema, edema, nodule, and bruise with a largest diameter greater than 120 mm.
g Moderate = causes discomfort and interferes with normal daily activities; Severe = incapacitating and completely prevents performing normal daily activities. This is based on the systemic AE categories of fatigue, muscle ache, headache, and fever.

Solicited and unsolicited adverse reactions observed from Day 0 through month 43 at a higher frequency (by at least 5%) in the BioThrax groups (IM and SC) as compared with the placebo (P) group were: headache (70.4% IM, 78.4% SC, 68.1% P); myalgia (72% IM, 76.1% SC, 50% P); and fatigue (70.1% IM, 76.8% SC, 60.8% P).

Post-Exposure Prophylaxis

A phase 3, open-label, uncontrolled, multi-center study evaluated the three-dose post-exposure prophylaxis BioThrax schedule (Week 0, 2, and 4) in 200 healthy adult subjects. The most common solicited adverse reactions reported 7 days after each vaccination comprised local reactions, including symptoms of lump, tenderness, and erythema. The most common solicited systemic reactions comprised fatigue, headache, and myalgia. Of the subjects that reported local and systemic solicited reactions, ≥ 98% required minimal or no treatment and resulted in little to no interference with subjects’ daily activity. The most common (> 2.0%) unsolicited related adverse reactions reported following at least one dose up to 100 days after the third dose were: headache (4.0%), fatigue (3.5%), skin hyperpigmentation (3.5%), decreased joint range of motion (2.5%), myalgia (2.5%). No deaths were reported and neither of the two SAEs reported were considered to be related to vaccination. There were no pregnancies reported or subject withdrawals from the study due to adverse events.

6.2 Postmarketing Experience

The following adverse events have been reported spontaneously. Since these events are reported voluntarily from a population of uncertain size, it is not always possible to reliably estimate their frequency or establish a causal relationship to drug exposure. The reports included below are listed due to one or more of the following factors: (1) seriousness of the event, (2) number of reports, or (3) strength of causal relationship to the drug.

- Blood and lymphatic system disorders
Lymphadenopathy
- Gastrointestinal disorders
Nausea
- Immune system disorders
Allergic reactions (including anaphylaxis, angioedema, rash, urticaria, pruritus, erythema multiforme, anaphylactoid reaction, and Stevens-Johnson syndrome)
- Nervous system disorders
Paresthesia, syncope, dizziness, tremor, ulnar nerve neuropathy
- Musculoskeletal, connective tissue, and bone disorders
Arthralgia, arthropathy, myalgia, rhabdomyolysis, alopecia
- General disorders and administration site conditions
Malaise, pain, cellulitis, flu-like symptoms
- Psychiatric disorders
Insomnia
- Skin and subcutaneous disorders
Pruritus, rash, urticaria
- Vascular disorders
Flushing

Infrequent reports were also received of multisystem disorders defined as chronic symptoms involving at least two of the following three categories: fatigue, mood-cognition, and musculoskeletal system.

7 DRUG INTERACTIONS

7.1 Ciprofloxacin

Co-administration of 0.5 mL BioThrax SC with oral ciprofloxacin in human subjects did not alter the pharmacokinetics of ciprofloxacin or the immunogenicity of BioThrax as measured by the anthrax lethal toxin neutralization assay. [see Clinical Studies (14.3)]

7.2 Concomitant Administration with Other Vaccines

The safety and efficacy of concomitant administration of BioThrax with other licensed vaccines has not been evaluated.

BioThrax should not be mixed with any other vaccine in the same syringe or vial. If BioThrax is to be given at the same time as another injectable vaccine(s), the vaccine(s) should be administered at different injection sites.

8 USE IN SPECIFIC POPULATIONS

8.1 Pregnancy

Risk Summary

All pregnancies have a risk of birth defect, loss, or other adverse outcomes. In clinically recognized pregnancies in the US general population, the estimated background risk of major birth defects is 2% to 4% and of miscarriage is 15% to 20%.

BioThrax can cause fetal harm when administered to a pregnant woman.

Human data on BioThrax administered to pregnant individuals are from the BioThrax observational study and pregnancy exposure registry. In the observational study there were more birth defects in infants born to individuals vaccinated with BioThrax in the first trimester compared with individuals vaccinated post pregnancy or individuals never vaccinated with BioThrax. Data from the BioThrax pregnancy exposure registry do not establish the presence or absence of vaccine-associated risks in pregnancy (see Human Data).

In a developmental toxicity study, female rabbits were administered a full human dose (0.5 mL) of BioThrax twice prior to mating and once during gestation. This study revealed no evidence of harm to the fetus, changes in reproductive performance, or adverse effects on post-natal development due to the vaccine (see Animal Data).

Data

Human Data

An observational study examined the rate of birth defects among 37,140 infants born to US military service personnel who received BioThrax prior to, during, and post pregnancy between 1998 and 2004. In this study, birth defects were slightly more common in first trimester-exposed infants (4.68%) when compared with infants of individuals vaccinated post pregnancy (3.85%) (odds ratio = 1.20; 95% confidence interval: 1.005, 1.43) or when compared with individuals never vaccinated with BioThrax (4.03%) (odds ratio = 1.20; 95% confidence interval: 1.02, 1.42)^1.

A pregnancy exposure registry was conducted in individuals who received BioThrax. Of 91 individuals who reported pregnancy outcomes, the majority of exposures were in the first trimester (n=89), and there were two infants with major birth defects (2.2%) and no miscarriages.

Animal Data

The effect of BioThrax on embryo-fetal and pre-weaning development was evaluated in a developmental toxicity study in rabbits. One group of rabbits was administered BioThrax twice prior to gestation and during the period of organogenesis (gestation Day 7). A second group of rabbits was administered BioThrax twice prior to gestation and on gestation Day 17. BioThrax was administered at 0.5 mL/rabbit/occasion, by intramuscular injection. No adverse effects on mating, fertility, pregnancy, parturition, lactation, embryo-fetal or pre-weaning development were observed. There were no vaccine-related fetal malformations or other evidence of teratogenesis noted in this study.

8.2 Lactation

Risk Summary

It is not known whether BioThrax is excreted in human milk. Human data are not available to assess the impact of the vaccine on milk production, its presence in breast milk, or its effects on the breastfed child. The developmental and health benefits of breastfeeding should be considered along with the mother's clinical need for BioThrax and any potential adverse effects on the breastfed child, or from the underlying maternal condition. For preventive vaccines, the underlying maternal condition is susceptibility to disease prevented by the vaccine.

8.4 Pediatric Use

Safety and effectiveness of BioThrax in individuals younger than 18 years of age have not been established.

8.5 Geriatric Use

Safety and effectiveness of BioThrax in individuals older than 65 years of age have not been established.

11 DESCRIPTION

BioThrax® (Anthrax Vaccine Adsorbed) is a sterile, milky-white injectable suspension for intramuscular or subcutaneous use made from cell-free filtrates of microaerophilic cultures of an avirulent, nonencapsulated strain of Bacillus anthracis. The production cultures are grown in a chemically defined protein-free medium consisting of a mixture of amino acids, vitamins, inorganic salts, and sugars. The final product, prepared from the sterile filtrate culture fluid contains proteins, including the 83kDa protective antigen (PA) protein, released during the growth period and contains no dead or live bacteria. The final product is formulated to contain 1.2 mg/mL aluminum, added as aluminum hydroxide in 0.85% sodium chloride. The final product is formulated to contain 25 mcg/mL benzethonium chloride and 100 mcg/mL formaldehyde, added as preservatives.

12 CLINICAL PHARMACOLOGY

12.1 Mechanism of Action

Anthrax is a zoonotic disease caused by the Gram-positive, spore-forming bacterium Bacillus anthracis. BioThrax induces antibodies raised against PA that may contribute to protection by neutralizing the activities of the cytotoxic lethal toxin and edema toxin of Bacillus anthracis.^2 Bacillus anthracis proteins other than PA may be present in BioThrax, but their contribution to protection has not been determined.

13 NONCLINICAL TOXICOLOGY

13.1 Carcinogenesis, Mutagenesis and Impairment of Fertility

BioThrax has not been evaluated for carcinogenicity, mutagenic potential, or male infertility in animals. BioThrax administered to female rabbits had no effect on fertility [see Use in Specific Populations (8.1)].

13.2 Animal Toxicology and/or Pharmacology

Since it is not feasible or ethical to conduct controlled clinical trials with anthrax, the efficacy of BioThrax in a post-exposure setting is based on studies in animals. Pre-exposure prophylaxis animal models were used to derive protective antibody thresholds to bridge animal efficacy and human immunogenicity data and predict efficacy in humans.

Pivotal efficacy animal studies were conducted in rabbits and nonhuman primates (NHPs). Animals received two IM vaccinations four weeks apart with serial dilutions of BioThrax and were subjected to lethal challenge on study day 70 with aerosolized B. anthracis spores at a target dose exceeding the 50% lethal dose by 200-fold. Serum samples were collected at various time points prior to challenge for immune response analysis via anthrax lethal toxin neutralizing antibody (TNA) assay. The relationship between pre-challenge serum TNA levels and survival was evaluated. Logistic regression analysis demonstrated that a 70% probability of survival was associated with a TNA NF50 (50% neutralization factor) level of 0.56 in rabbits and 0.29 in NHPs.

The ability of BioThrax to increase survival after the cessation of the post-exposure antimicrobial treatment, as compared with antimicrobial treatment alone, was investigated in two post-exposure animal model studies. In these studies, rabbits were challenged via inhalation with aerosolized B. anthracis spores and subsequently treated with levofloxacin administered via oral gavage once daily for 7 days starting at 6-12 hours post-exposure, with or without two intramuscular injections of BioThrax one week apart. Survival among animals that received both antimicrobial treatment and vaccination was between 70 – 100% and increased in a vaccine dose-dependent manner. In contrast, only 44% and 23% survival was observed among animals that received antimicrobial treatment only in the first and the second study, respectively (p < 0.0006 and p < 0.004, respectively). [see Clinical Studies (14.2)]

14 CLINICAL STUDIES

14.1 Pre-Exposure Prophylaxis

A controlled field study using an earlier version of a protective antigen-based anthrax vaccine developed in the 1950’s and supplied by G. G. Wright and associates of the U.S. Army Chemical Corps, Fort Detrick, Frederick, MD, that consisted of an aluminum potassium sulfate-precipitated cell-free filtrate from an aerobic culture, was conducted from 1955-1959.^3 This study included 1,249 workers [379 received anthrax vaccine, 414 received placebo, 116 received incomplete inoculations (with either vaccine or placebo) and 340 were in the observational group (no treatment)] in four mills in the northeastern United States that processed imported animal hides. The anthrax vaccine was administered subcutaneously at 0, 2, 4 weeks, 6, 12, 18 months. Prior to vaccination, the yearly average number of human anthrax cases (both cutaneous and inhalational) was 1.2 cases per 100 employees in these mills. During the trial, 26 cases of anthrax were reported across the four mills – 5 inhalation and 21 cutaneous. Of the five inhalation cases (four of which were fatal), two received placebo and three were in the observational group. Of the 21 cutaneous cases, 15 received placebo, three were in the observational group, and three received anthrax vaccine. Of those three cases in the vaccine group, one case occurred just prior to administration of the scheduled third dose, one case occurred 13 months after an individual received the third of the scheduled 6 doses (but no subsequent doses), and one case occurred prior to receiving the scheduled fourth dose of vaccine. The calculated efficacy of the vaccine to prevent all types of anthrax disease, regardless of the route of exposure or clinical manifestations, was 92.5% (lower 95% Confidence Interval (CI) = 65%).

Between 1962 and 1974, the Centers for Disease Control and Prevention (CDC) collected surveillance data on the occurrence of anthrax disease in mill workers or those living near mills in the United States.^4,5 In that time period, individuals received either BioThrax or the earlier protective antigen-based anthrax vaccine used in the field trial described above. Of the 27 reported cases of anthrax, 24 cases occurred in unvaccinated individuals. In vaccinated individuals one case occurred after the person had been given one dose of anthrax vaccine and two cases occurred after individuals had been given two doses of anthrax vaccine. No documented cases of anthrax were reported for individuals who had received at least three doses of the originally licensed six-dose series of anthrax vaccine.

Between 2002 and 2007, a prospective double-blinded, randomized, placebo-controlled and active-controlled study was conducted to evaluate the impact on safety and immunogenicity on changing the administration route from SC to IM, and reducing the number of doses. This study enrolled 1,564 healthy civilian men and women between the ages of 18 and 61. A total of 1,563 subjects received at least one dose (one subject withdrew consent prior to the first injection). Subjects were randomized to one of six groups. See Table 1.

Using an Enzyme-Linked Immunosorbent Assay (ELISA), Immunoglobulin G (IgG) antibodies directed against anthrax protective antigen (PA) were measured at the Week 8 and Months 7, 13, 19, 31, and 43 time points. The three primary immunogenicity endpoints were: (1) Geometric Mean Concentration (GMC) (mcg/mL), (2) Geometric Mean Titer (GMT), and (3) percentage with 4-fold rise in anti-PA antibody titer from baseline.

The criteria for noninferiority of comparisons based on ratios of GMCs and GMTs and differences in the rates of 4-fold rise in antibody titer were defined as follows:

Mean antibody concentration ratio: noninferiority was achieved when the upper bound of the 95% confidence limit was < 1.5
Mean antibody titer ratio: noninferiority was achieved when the upper bound of the 95% confidence limit was < 1.5
4-fold rise in antibody titer: noninferiority was achieved when the upper bound of the 95% confidence limit was < 0.10

To compare the originally licensed 6-dose SC schedule (0, 2, 4 weeks and 6, 12, and 18 months) versus a 3-dose IM primary series (at 0, 1, and 6 months), noninferiority analyses were performed for all three primary immunogenicity endpoints. This evaluation compared the immune response at Month 7 for Group C (COM, where COM is Combined, as described in 6.1) to Month 19 for Group A (TRT-8SC, where TRT is Treatment) and Group B (TRT-8IM). Noninferiority was demonstrated for all analyses (See Table 3). These results support a 3 dose primary series of BioThrax administered IM at 0, 1 and 6 months, followed by booster doses at 12 and 18 months and at 1-year intervals thereafter to maintain protective immunity.

The Month 7 antibody levels of Group A (TRT-8SC) were noninferior to Month 13 and 19 antibody levels after a 0, 2, 4 week and 6 month primary SC series followed by SC booster injections at 12 and 18 months (see Table 3). These results support a 4 dose SC primary series of BioThrax administered at weeks 0, 2, 4, and at 6 months followed by booster doses at 12 and 18 months after initiation of the series, and at 1-year intervals thereafter to maintain protective immunity.

Catch-Up Administration for Delayed or Missed Doses

In subjects who did not receive booster doses at 12, 18, and 30 months, PA antibody levels decline over time following the third dose of BioThrax administered intramuscularly at 6 months (Group F; 4IM; 0, 1, 6, and 42 months). In the absence of booster doses it is not known whether these individuals are adequately protected between 12 months and receipt of a booster dose at 42 months. One month following a dose of BioThrax at 42 months the immune response for Group F met the criteria for noninferiority relative to Group A (8SC) for all three primary immunogenicity endpoints (see Table 3). The optimal schedule for further intramuscular booster doses among persons administered a single booster dose at 42 months following completion of a three-dose primary series at 0, 1, and 6 months is not known.

Table 3 Primary Immunogenicity Endpoints (According to Protocola)
 | Week 4 | Week 8 | Month 7 | Month 13 | Month 19 | Month 31 | Month 43
Anti-PA Specific IgG GMC, mcg/mL
 | n; GMC; 95%CI | n; GMC; 95%CI | n; GMC; 95%CI | n; GMC; 95%CI | n; GMC; 95%CI | n; GMC; 95%CI | n; GMC; 95%CI
TRT-8SC; Group A | 242; 49.72; (43.32, 57.06) | 235; 94.29; (82.08, 108.31) | 219; 201.14; (174.71, 231.56) | 203; 201.67; (174.77, 232.71) | 190; 193.45; (167.29, 223.69) | 167; 250.07; (215.38, 290.34) | 144; 216.83; (185.80, 253.05)
TRT-7IMb; Group D | 723; 2.63; (2.39, 2.89) | 698; 46.39 (42.18, 51.01) | 636; 206.09; (187.14, 226.96) | 203; 229.86; (203.20, 260.02) | 192; 204.95; (180.82, 232.29) | 169; 263.13; (231.09, 299.61) | 139; 254.80; (222.03, 292.40)
TRT-5IMb; Group E |  |  |  | 399; 28.64; (25.79, 31.81) | 174; 293.60; (258.30, 333.73) | 153; 33.68; (29.48, 38.48) | 141; 310.02; (270.49, 355.33)
TRT-4IMb; Group F |  |  |  |  | 193; 13.71; (12.11, 15.53) | 179; 7.80; (6.87, 8.86) | 157; 433.20; (379.58, 494.40)
Anti-PA Specific IgG GMT
 | n; GMT; 95% CI | n; GMT; 95% CI | n; GMT; 95% CI | n; GMT; 95% CI | n; GMT; 95% CI | n; GMT; 95% CI | n; GMT; 95% CI
TRT-8SC; Group A | 242; 565.16; (492.57, 648.45) | 235; 1048.50; (913.05, 1204.05) | 219; 2211.94; (1921.78, 2545.90) | 203; 2184.59; (1893.62, 2520.26) | 190; 2080.89; (1799.87, 2405.79) | 167; 2677.97; (2306.82, 3108.83) | 144; 2282.36; (1955.79, 2663.45)
TRT-7IMb; Group D | 723; 36.61; (33.32, 40.23) | 698; 514.57; (468.08, 565.68) | 636; 2257.09; (2050.12, 2484.94) | 203; 2546.81; (2251.11, 2881.35) | 192; 2254.56; (1988.85, 2555.75) | 169; 2867.88; (2518.14, 3266.19) | 139; 2760.35; (2404.66, 3168.64)
TRT-5IMb; Group E |  |  |  | 399; 296.08; (266.67, 328.74) | 174; 3167.26; (2785.88, 3600.85) | 153; 348.89; (305.33, 398.66) | 141; 3286.41; (2866.50, 3767.83)
TRT-4IMb; Group F |  |  |  |  | 193; 135.30; (119.44, 153.26) | 179; 79.63; (70.10, 90.44) | 157; 4683.79; (4102.99, 5346.80)
4-fold response
 | n; 4-fold response; 95% CI | n; 4-fold response; 95% CI | n; 4-fold response; 95% CI | n; 4-fold response; 95% CI | n; 4-fold response; 95% CI | n; 4-fold response; 95% CI | n; 4-fold response; 95% CI
TRT-8SC; Group A | 242; 80.99; (75.47, 85.73) | 235; 94.89; (91.25, 97.33) | 219; 98.63; (96.05, 99.72) | 203; 99.51; (97.29, 99.99) | 190; 98.95; (96.25, 99.87) | 167; 100.00; (97.82, 100.00) | 144; 100.00; (97.47, 100.00)
TRT-7IMb; Group D | 723; 4.15; (2.82, 5.87) | 698; 78.80; (75.57, 81.77) | 636; 97.80; (96.33, 98.79) | 203; 100.00; (98.20, 100.00) | 192; 98.96; (96.29, 99.87) | 169; 100.00; (97.84, 100.00) | 139; 100.00; (97.38, 100.00)
TRT-5IMb; Group E |  |  |  | 399; 60.40; (55.41, 65.23) | 174; 99.43; (96.84, 99.99) | 153; 63.40; (55.24, 71.03) | 141; 99.29; (96.11, 99.98)
TRT-4IMb; Group F |  |  |  |  | 193; 37.82; (30.96, 45.07) | 179; 22.35; (16.47, 29.16) | 157; 99.36; (96.50, 99.98)
CI: Confidence Interval;
a According to Protocol (ATP): [NCT00119067] To be included in the ATP population at a particular timepoint, a participant must have: (a) received all injections up through that timepoint, (b) received these injections within the windows defined by protocol, (c) received the correct agent administered by the correct route according to subject's assigned study arm, (d) received the correct injection volume. A shot of 0.3 mL or greater is considered valid.
b Groups TRT-7IM, -5IM, and -4IM combined as group TRT-COM (combined) through Month 7 of the study, GMC: geometric mean concentration. GMT: geometric mean titer. IM: Intramuscular; SC: Subcutaneous, TRT: treatment.

14.2 Post-Exposure Prophylaxis

Based on the rabbit model-derived TNA threshold [see Nonclinical Toxicology (13.2)], a pivotal clinical study was conducted to evaluate the immunogenicity and safety of a post-exposure SC administration schedule of BioThrax in healthy adults following 3 doses at 0, 2, and 4 weeks. Two hundred subjects were enrolled and followed for 128 days. The primary objective was to assess immunogenicity using TNA following the completion of three SC doses of BioThrax. The primary immunogenicity endpoint was the proportion of subjects achieving a threshold TNA NF50 value ≥0.56 at Day 63, 5 weeks after the third vaccination. Success was concluded if the lower bound of the 2-sided 95% CI of the proportion of human subjects achieving the TNA NF50 threshold was ≥ 40%.

Overall, 71.2% of subjects achieved an NF50 value ≥0.56 on Day 63 in the pivotal study. The lower bound of the 95% CI was 64.1%. (See Table 4.)

In a separate analysis of the pivotal clinical study using the threshold associated with a 70% probability of survival in NHPs, 93.5% of subjects achieved an NF50 value ≥0.29 on Day 63 (Table 4). The lower bound of the 95% CI was 88.9% (Table 4). The bridging of human immunogenicity data to the NHP study was supportive of the primary analysis comparing human threshold data with rabbit survival. [see Nonclinical Toxicology (13.2)]

Table 4 Proportion of Subjects Achieving TNA NF50 Thresholda in the Pivotal Clinical Study (PP Populationb)
Animal Model | Time Point Human/ Animal | n | Human GMT TNA NF50 (SD) | Animal TNA NF50 Thresholdc | Number of Subjects Meeting Threshold | Proportion of Subjects Meeting Threshold, (%) | Proportion of Subjects Meeting Threshold, 95% CI (%)d
Rabbite | Day 63/ Day 69 | 184 | 0.86 (2.09) | 0.56 | 131 | 71.2 | 64.1; 77.6
Non-human Primatef | Day 63/ Day 70 | 184 | 0.86 (2.09) | 0.29 | 172 | 93.5 | 88.9; 96.6
CI = confidence interval; NF50 = 50% neutralization factor; PP = per protocol; SD = standard deviation; TNA = toxin neutralizing antibody.
Note: Sample size (N) and denominators used for percentages are based on the number of subjects meeting the PP criteria at specified day(s).
a TNA NF50 threshold is defined as the TNA NF50 value associated with 70% survival in the animal challenge studies.
b Human data are from the pivotal clinical study (NCT01491607).
c A logistic regression model with log10-transformed TNA NF50 values as the predictor and survival as the response is used to derive the TNA NF50 threshold associated with 70% probability of survival in rabbits and non-human primates, respectively.
d 95% CI (lower bound; upper bound) is calculated with the exact (Clopper-Pearson) method.
e The proportion of subjects achieving a TNA NF50 response at Day 63 that met or exceeded the TNA NF50 threshold in the rabbit model at Day 69 comprised the primary immunogenicity endpoint.
f Comparison of the human TNA NF50 response at Day 63 with the NHP TNA NF50 threshold at Day 70 was defined as an immunogenicity endpoint and was supportive of the bridging of human immunogenicity data to rabbit survival.

14.3 Non-Interference of Post-Exposure Prophylaxis Vaccination and Antimicrobials When Used Concurrently

An open-label study was conducted to evaluate the potential impact 0.5 mL BioThrax administered SC at 0, 2 and 4 weeks had on the pharmacokinetics of ciprofloxacin in healthy adult male and female subjects (N=154). It also evaluated the potential impact of ciprofloxacin on immunogenicity of BioThrax two weeks following the last BioThrax dose.

Co-administration of 0.5 mL BioThrax SC with oral ciprofloxacin in human subjects did not alter the pharmacokinetics of ciprofloxacin or the immunogenicity of BioThrax as measured by the anthrax lethal toxin neutralization assay.

15 REFERENCES

1. Ryan MA, Smith TC, Sevick CJ, Honner WK, Loach RA, Moore CA, Erickson JD. 2008. Birth defects among infants born to women who received anthrax vaccine in pregnancy. Am J Epidemiol, 168:434-442.
2. Brachman P, Friedlander A, Grabenstein J. 2008. Anthrax Vaccine. In: Vaccines, Fifth Edition, Plotkin, S.A.: Orenstein W.A. and Offit P.A. (eds.), 111-126
3. Brachman, PS, Gold H, Plotkin SA, Fekety FR, Werrin M, Ingraham NR. 1962. Field evaluation of a human anthrax vaccine. Amer. J. Public Health, 52:632-645.
4. Food and Drug Administration, 2005, Biological Products; Bacterial Vaccines and Toxoids; Implementation of Efficacy Review; Anthrax Vaccine Adsorbed; Final Order. FDA Federal Register 2005; 70(242): 75180-75198.
5. Food and Drug Administration. Biological Products; Bacterial vaccines and toxoids; Implementation of efficacy review. Federal Register (December 13, 1985), 50(240):51002-51117.

16 HOW SUPPLIED/STORAGE AND HANDLING

16.1 How Supplied

BioThrax is supplied in 5 mL multiple-dose vials containing ten 0.5 mL doses.

NDC 64678-211-05 (vial), 64678-211-01 (carton)

The stopper of the vial contains natural rubber latex and may cause allergic reactions in latex sensitive individuals.

16.2 Storage and Handling

Store at 2°C to 8°C (36°F to 46°F). Do not freeze. Discard if product has been frozen. Do not use BioThrax after the expiration date printed on the label.

- Once the stopper of the multiple-dose vial has been pierced, discard the vial within 28 days.
- Write the date of discard (28 days after the vial stopper was first pierced) on the vial and the carton in the designated area.
- Between uses, store the multiple-dose vial at 2°C to 8°C (36°F to 46°F).
- The date of discard should not exceed the manufacturer’s expiration date printed on the label.

17 PATIENT COUNSELING INFORMATION

See FDA-approved patient labeling (Patient Information).

Advise women of the potential risk to the fetus. [see Use in Specific Populations (8.1)]

Inform patients of the benefits and risks of immunization with BioThrax.

Instruct patients to report any serious adverse reaction to their health care provider.
Manufactured by:

Emergent BioDefense Operations Lansing LLC
Lansing, MI 48906
US License No. 1755
BioThrax® is a registered trademark of Emergent BioDefense Operations Lansing LLC

Patient Information

BioThrax® (Anthrax Vaccine Adsorbed)

for intramuscular or subcutaneous use

Please read this Patient Information summary carefully before you get this shot. This summary does not take the place of talking with your healthcare provider about BioThrax. If you have questions or would like more information, please talk with your healthcare provider.

What is BioThrax?

- BioThrax is a vaccine licensed by the FDA to protect against anthrax disease in persons 18 through 65 years of age:
  - It can be used before exposure to anthrax to protect people at high risk of getting the disease.
  - It can be used after exposure to anthrax, along with antibiotics, to protect people from getting the disease.
- BioThrax may not protect all people who get the vaccine.
- How well BioThrax works when given after exposure to anthrax has been studied only in animals. It has not been studied in humans because there are not enough people who get the disease naturally, and it is not ethical to expose people to anthrax on purpose to find out how well BioThrax works.
- The safety of BioThrax was studied in healthy adults.

Who should not get BioThrax?

You should not get BioThrax if you have a history of severe allergic reaction to any ingredient of the vaccine, including aluminum hydroxide, benzethonium chloride, and formaldehyde or had a serious reaction after getting BioThrax previously.

What should I tell my healthcare provider before getting BioThrax?

- If you may be pregnant, plan to get pregnant soon, or are nursing a baby.
- About medicines that you take, including over-the-counter medicines and supplements.
- About immune problems you have, including steroid treatments and cancer treatments.
- About blood clotting problems or if you take “blood thinners.”
- If you are allergic to latex.

What if I discover I was pregnant at the time I got BioThrax?

- Inform your healthcare provider

How is BioThrax given?

BioThrax is given as an injection in the muscle or under the skin.

After getting the first shot, you should come back for the next shots on the schedule given to you by your health care provider. It is important that you get all your shots to get the best protection.

If you get BioThrax because you may have been exposed to anthrax, it is important that you also take antibiotics for 60 days.

What are the possible or reasonably likely side effects of BioThrax?

The most common side effects of BioThrax are:

- Pain, tenderness, redness, bruising, or problems moving the arm in which you got the shot
- Muscle aches
- Headaches
- Fatigue
- Fainting

Tell your healthcare provider about any side effects that concern you. Your healthcare provider can give you a complete list of side effects available to healthcare professionals.

You may report side effects to FDA by calling 1-800-822-7967 or to the website www.vaers.hhs.gov. You may also report side effects directly to Emergent BioSolutions at 1-800-768-2304 or at medicalinformation@ebsi.com.

What are the ingredients in BioThrax?

BioThrax does not contain live bacteria. BioThrax contains non-infectious proteins, aluminum hydroxide, benzethonium chloride and formaldehyde (as preservatives).

The vial stopper contains natural rubber latex.

Manufactured by:
Emergent BioDefense Operations Lansing LLC
Lansing, MI 48906, USA
License No. 1755

Issued: 11/2025

BioThrax DHCP Letter – 28-Day Discard Statement

11/2025

IMPORTANT PRESCRIBING INFORMATION

Subject: Important Labeling Update for BioThrax® (Anthrax Vaccine Adsorbed): 28-Day Discard After Vial Puncture Instructions

Dear Healthcare Provider:

The purpose of this letter is to inform you of an important update to the labeling of BioThrax® (Anthrax Vaccine Adsorbed), specifically regarding the storage and handling of the multiple-dose vial once it has been pierced.

Effective immediately, the following information has been added to the United States Prescribing Information (USPI), Section 2.2 Administration to state:
Once the stopper of the multiple-dose vial has been pierced, discard the vial within 28 days.

Additional information on the 28-day discard date has been included in Section 16.2 Storage and Handling, to state:

- Once the stopper of the multiple-dose vial has been pierced, discard the vial within 28 days.
- Between uses, store the multiple-dose vial at 2°C to 8°C (36°F to 46°F).
- The date of discard should not exceed the manufacturer’s expiration date printed on the label.

Information has also been added to Section 16.2 Storage and Handling to clarify that product should be discarded if it has been frozen.

Healthcare Provider Action

To ensure proper storage and handling of BioThrax®, healthcare providers are instructed to:

- Ensure that the multiple-dose vial is stored at 2°C to 8°C (36°F to 46°F) between uses
- Discard the vial within 28 days of first puncture
- Ensure that the discard date does not exceed the expiration date printed on the vial
- Ensure all clinical staff are informed and trained on these instructions

Reporting Adverse Events

Report adverse events following BioThrax® administration to FDA by calling 1-800-822-7967 or to the website www.vaers.hhs.gov. You may also report side effects directly to Emergent BioSolutions at 1-800-768-2304 or at medicalinformation@ebsi.com.

If you require further guidance regarding the information contained in this letter, please contact medicalinformation@ebsi.com or call 1-888-483-9053.

This letter is not intended as a complete description of the benefits and risks related to the use of BioThrax®; please refer to the enclosed full prescribing information.
Sincerely,
Scott White, M.D.
Vice President, Head of Clinical Development
Interim Head of Global Patient Safety
Emergent BioSolutions

Principal Display Panel - BioThrax Vaccine - 5mL Vial Label

NDC 64678-211-05

ANTHRAX
VACCINE
ADSORBED

BioThrax®

Ten doses of 0.5 mL each

Rx Only

U.S. License No. 1755

LBL040761-01

EMERGENT®

Store at 2-8° C (36-46°F) Do Not Freeze

Shake well immediately before use

Discard after: _______/_______/______

Mfd. by Emergent BioDefense Lansing, MI 48906 USA

Principal Display Panel - BioThrax Vaccine - 5mL Vial Carton

NDC 64678-211-01

ANTHRAX
VACCINE
ADSORBED

BioThrax®

EMERGENT®

Manufactured by Emergent BioDefense Operations Lansing LLC

Lansing, Michigan 48906 U.S.A.

U.S. License No. 1755

Rx Only